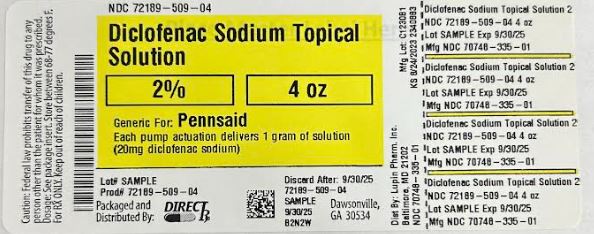 DRUG LABEL: Diclofenac Sodium Topical Solution
NDC: 72189-509 | Form: SOLUTION
Manufacturer: Direct_Rx
Category: prescription | Type: HUMAN PRESCRIPTION DRUG LABEL
Date: 20230926

ACTIVE INGREDIENTS: DICLOFENAC SODIUM 20 mg/1 g
INACTIVE INGREDIENTS: WATER; DIMETHYL SULFOXIDE; HYDROXYPROPYL CELLULOSE (1600000 WAMW); PROPYLENE GLYCOL; ALCOHOL

Diclofenac Sodium Topical Solution

BOXED WARNING

Cardiovascular Thrombotic Events - Nonsteroidal anti-inflammatory drugs (NSAIDs) cause an increased risk of serious cardiovascular thrombotic events, including myocardial infarction, and stroke ...

WARNING: RISK OF SERIOUS CARDIOVASCULAR AND GASTROINTESTINAL EVENTS

Cardiovascular Thrombotic Events

Nonsteroidal anti-inflammatory drugs (NSAIDs) cause an increased risk of serious cardiovascular thrombotic events, including myocardial infarction, and stroke, which can be fatal. This risk may occur early in treatment and may increase with duration of use. [see Warnings and Precautions (5.1)] .
Diclofenac sodium topical solution is contraindicated in the setting of coronary artery bypass graft (CABG) surgery [see Contraindications (4) and Warnings and Precautions (5.1)] .

Gastrointestinal Bleeding, Ulceration, and Perforation

NSAIDs cause an increased risk of serious gastrointestinal (GI) adverse events including bleeding, ulceration, and perforation of the stomach or intestines, which can be fatal. These events can occur at any time during use and without warning symptoms. Elderly patients and patients with a prior history of peptic ulcer disease and/or GI bleeding are at greater risk for serious GI events [see Warnings and Precautions (5.2)] .

INDICATIONS AND USAGE

Diclofenac sodium topical solution is indicated for the treatment of the pain of osteoarthritis of the knee(s).

DOSAGE AND ADMINISTRATION

2.1 General Dosing Instructions

Use the lowest effective dosage for the shortest duration consistent with individual patient treatment goals [see Warnings and Precautions (5.2)].

For relief of the pain of osteoarthritis (OA) of the knee(s), the recommended dose is 40 mg of diclofenac sodium (2 pump actuations) on each painful knee, 2 times a day.

Apply diclofenac sodium topical solution to clean, dry skin.

The pump must be primed before first use. Instruct patients to fully depress the pump mechanism (actuation) 4 times while holding the bottle in an upright position. This portion should be discarded to ensure proper priming of the pump. No further priming of the bottle should be required.

After the priming procedure, diclofenac sodium topical solution is properly dispensed by completely depressing the pump 2 times to achieve the prescribed dosage for one knee. Deliver the product directly into the palm of the hand and then apply evenly around front, back, and sides of the knee.

Application of diclofenac sodium topical solution in an amount exceeding or less than the recommended dose has not been studied and is therefore not recommended.

2.2 Special Precautions

Avoid showering/bathing for at least 30 minutes after the application of diclofenac sodium topical solution to the treated knee.
Wash and dry hands after use.
Do not apply diclofenac sodium topical solution to open wounds.
Avoid contact of diclofenac sodium topical solution with eyes and mucous membranes.
Do not apply external heat and/or occlusive dressings to treated knees.
Avoid wearing clothing over the diclofenac sodium topical solution-treated knee(s) until the treated knee is dry.
Protect the treated knee(s) from natural and artificial sunlight.
Wait until the treated area is dry before applying sunscreen, insect repellant, lotion, moisturizer, cosmetics, or other topical medication to the same knee you have just treated with diclofenac sodium topical solution.
Until the treated knee(s) is completely dry, avoid skin-to-skin contact between other people and the treated knee(s).
Do not use combination therapy with diclofenac sodium topical solution and an oral NSAID unless the benefit outweighs the risk and conduct periodic laboratory evaluations.

DOSAGE FORMS AND STRENGTHS

Diclofenac sodium topical solution: 2% w/w

CONTRAINDICATIONS

Diclofenac sodium topical solution is contraindicated in the following patients:

Known hypersensitivity (e.g., anaphylactic reactions and serious skin reactions) to diclofenac or any components of the drug product [see Warnings and Precautions (5.7, 5.9)]
History of asthma, urticaria, or other allergic-type reactions after taking aspirin or other NSAIDs. Severe, sometimes fatal, anaphylactic reactions to NSAIDs have been reported in such patients [see Warnings and Precautions (5.7, 5.8)]
In the setting of coronary artery bypass graft (CABG) surgery [see Warnings and Precautions (5.1)]

WARNINGS AND PRECAUTIONS

5.1 Cardiovascular Thrombotic Events

Clinical trials of several COX-2 selective and nonselective NSAIDs of up to three years duration have shown an increased risk of serious cardiovascular (CV) thrombotic events, including myocardial infarction (MI), and stroke, which can be fatal. Based on available data, it is unclear that the risk for CV thrombotic events is similar for all NSAIDs. The relative increase in serious CV thrombotic events over baseline conferred by NSAID use appears to be similar in those with and without known CV disease or risk factors for CV disease. However, patients with known CV disease or risk factors had a higher absolute incidence of excess serious CV thrombotic events, due to their increased baseline rate. Some observational studies found that this increased risk of serious CV thrombotic events began as early as the first weeks of treatment. The increase in CV thrombotic risk has been observed most consistently at higher doses.

To minimize the potential risk for an adverse CV event in NSAID-treated patients, use the lowest effective dose for the shortest duration possible. Physicians and patients should remain alert for the development of such events, throughout the entire treatment course, even in the absence of previous CV symptoms. Patients should be informed about the symptoms of serious CV events and the steps to take if they occur.

There is no consistent evidence that concurrent use of aspirin mitigates the increased risk of serious CV thrombotic events associated with NSAID use. The concurrent use of aspirin and an NSAID, such as diclofenac, increases the risk of serious gastrointestinal (GI) events [see Warnings and Precautions (5.2)].

Status Post Coronary Artery Bypass Graft (CABG) Surgery

Two large, controlled, clinical trials of a COX-2 selective NSAID for the treatment of pain in the first 10-14 days following CABG surgery found an increased incidence of myocardial infarction and stroke. NSAIDs are contraindicated in the setting of CABG [see Contraindications (4)].

Post-MI Patients

Observational studies conducted in the Danish National Registry have demonstrated that patients treated with NSAIDs in the post-MI period were at increased risk of reinfarction, CV-related death, and all-cause mortality beginning in the first week of treatment. In this same cohort, the incidence of death in the first year post-MI was 20 per 100 person years in NSAID-treated patients compared to 12 per 100 person years in non-NSAID exposed patients. Although the absolute rate of death declined somewhat after the first year post-MI, the increased relative risk of death in NSAID users persisted over at least the next four years of follow-up.

Avoid the use of diclofenac sodium topical solution in patients with a recent MI unless the benefits are expected to outweigh the risk of recurrent CV thrombotic events. If diclofenac sodium topical solution is used in patients with a recent MI, monitor patients for signs of cardiac ischemia.

5.2 Gastrointestinal Bleeding, Ulceration, and Perforation

NSAIDs, including diclofenac, cause serious gastrointestinal (GI) adverse events including inflammation, bleeding, ulceration, and perforation of the esophagus, stomach, small intestine, or large intestine, which can be fatal. These serious adverse events can occur at any time, with or without warning symptoms, in patients treated with NSAIDs. Only one in five patients who develop a serious upper GI adverse event on NSAID therapy is symptomatic. Upper GI ulcers, gross bleeding, or perforation caused by NSAIDs occurred in approximately 1% of patients treated for 3-6 months, and in about 2%-4% of patients treated for one year. However, even short-term NSAID therapy is not without risk.

Risk Factors for GI Bleeding, Ulceration, and Perforation

Patients with a prior history of peptic ulcer disease and/or GI bleeding who used NSAIDs had a greater than 10-fold increased risk for developing a GI bleed compared to patients without these risk factors. Other factors that increase the risk of GI bleeding in patients treated with NSAIDs include longer duration of NSAID therapy; concomitant use of oral corticosteroids, aspirin, anticoagulants, or selective serotonin reuptake inhibitors (SSRIs); smoking; use of alcohol; older age; and poor general health status. Most postmarketing reports of fatal GI events occurred in elderly or debilitated patients. Additionally, patients with advanced liver disease and/or coagulopathy are at increased risk for GI bleeding.

Strategies to Minimize the GI Risks in NSAID-treated patients

Use the lowest effective dosage for the shortest possible duration.
Avoid administration of more than one NSAID at a time.
Avoid use in patients at higher risk unless benefits are expected to outweigh the increased risk of bleeding. For such patients, as well as those with active GI bleeding, consider alternate therapies other than NSAIDs.
Remain alert for signs and symptoms of GI ulceration and bleeding during NSAID therapy.
If a serious GI adverse event is suspected, promptly initiate evaluation and treatment, and discontinue diclofenac sodium topical solution until a serious GI adverse event is ruled out.
In the setting of concomitant use of low-dose aspirin for cardiac prophylaxis, monitor patients more closely for evidence of GI bleeding [see Drug Interactions (7)].

5.3 Hepatotoxicity

In clinical trials of oral diclofenac containing products, meaningful elevations (i.e., more than 3 times the ULN) of AST (SGOT) occurred in about 2% of approximately 5,700 patients at some time during diclofenac treatment (ALT was not measured in all studies).

In a large, open-label, controlled trial of 3,700 patients treated with oral diclofenac for 2-6 months, patients were monitored first at 8 weeks and 1,200 patients were monitored again at 24 weeks. Meaningful elevations of ALT and/or AST occurred in about 4% of 3,700 patients and included marked elevations (greater than 8 times the ULN) in about 1% of the 3,700 patients. In that open-label study, a higher incidence of borderline (less than 3 times the ULN), moderate (3 to 8 times the ULN), and marked (greater than 8 times the ULN) elevations of ALT or AST was observed in patients receiving diclofenac when compared to other NSAIDs. Elevations in transaminases were seen more frequently in patients with osteoarthritis than in those with rheumatoid arthritis.

Almost all meaningful elevations in transaminases were detected before patients became symptomatic. Abnormal tests occurred during the first 2 months of therapy with oral diclofenac in 42 of the 51 patients in all trials who developed marked transaminase elevations.

In postmarketing reports, cases of drug-induced hepatotoxicity have been reported in the first month, and in some cases, the first 2 months of NSAID therapy, but can occur at any time during treatment with diclofenac.

Postmarketing surveillance has reported cases of severe hepatic reactions, including liver necrosis, jaundice, fulminant hepatitis with and without jaundice, and liver failure. Some of these reported cases resulted in fatalities or liver transplantation.

In a European retrospective population-based, case-controlled study, 10 cases of oral diclofenac associated drug-induced liver injury with current use compared with non-use of diclofenac were associated with a statistically significant 4-fold adjusted odds ratio of liver injury. In this particular study, based on an overall number of 10 cases of liver injury associated with diclofenac, the adjusted odds ratio increased further with female gender, doses of 150 mg or more, and duration of use for more than 90 days.

Physicians should measure transaminases at baseline and periodically in patients receiving long-term therapy with diclofenac, because severe hepatotoxicity may develop without a prodrome of distinguishing symptoms. The optimum times for making the first and subsequent transaminase measurements are not known. Based on clinical trial data and postmarketing experiences, transaminases should be monitored within 4 to 8 weeks after initiating treatment with diclofenac. However, severe hepatic reactions can occur at any time during treatment with diclofenac.

If abnormal liver tests persist or worsen, if clinical signs and/or symptoms consistent with liver disease develop, or if systemic manifestations occur (e.g., eosinophilia, rash, abdominal pain, diarrhea, dark urine, etc.), diclofenac sodium topical solution should be discontinued immediately.

Inform patients of the warning signs and symptoms of hepatotoxicity (e.g., nausea, fatigue, lethargy, diarrhea, pruritus, jaundice, right upper quadrant tenderness, and "flu-like" symptoms). If clinical signs and symptoms consistent with liver disease develop, or if systemic manifestations occur (e.g., eosinophilia, rash, etc.), discontinue diclofenac sodium topical solution immediately, and perform a clinical evaluation of the patient.

To minimize the potential risk for an adverse liver-related event in patients treated with diclofenac sodium topical solution, use the lowest effective dose for the shortest duration possible. Exercise caution when prescribing diclofenac sodium topical solution with concomitant drugs that are known to be potentially hepatotoxic (e.g., acetaminophen, antibiotics, antiepileptics).

5.4 Hypertension

NSAIDs, including diclofenac, can lead to new onset of hypertension or worsening of preexisting hypertension, either of which may contribute to the increased incidence of CV events. Patients taking angiotensin converting enzyme (ACE) inhibitors, thiazide diuretics, or loop diuretics may have impaired response to these therapies when taking NSAIDs [see Drug Interactions (7)].

Monitor blood pressure (BP) during the initiation of NSAID treatment and throughout the course of therapy.

5.5 Heart Failure and Edema

The Coxib and traditional NSAID Trialists' Collaboration meta-analysis of randomized controlled trials demonstrated an approximately two-fold increase in hospitalizations for heart failure in COX-2 selective treated patients and nonselective NSAID-treated patients compared to placebo-treated patients. In a Danish National Registry study of patients with heart failure, NSAID use increased the risk of MI, hospitalization for heart failure, and death.

Additionally, fluid retention and edema have been observed in some patients treated with NSAIDs. Use of diclofenac may blunt the CV effects of several therapeutic agents used to treat these medical conditions (e.g., diuretics, ACE inhibitors, or angiotensin receptor blockers [ARBs]) [see Drug Interactions (7)].

Avoid the use of diclofenac sodium topical solution in patients with severe heart failure unless the benefits are expected to outweigh the risk of worsening heart failure. If diclofenac sodium topical solution is used in patients with severe heart failure, monitor patients for signs of worsening heart failure.

5.6 Renal Toxicity and Hyperkalemia

Renal Toxicity

Long-term administration of NSAIDs has resulted in renal papillary necrosis and other renal injury.

Renal toxicity has also been seen in patients in whom renal prostaglandins have a compensatory role in the maintenance of renal perfusion. In these patients, administration of an NSAID may cause a dose-dependent reduction in prostaglandin formation and, secondarily, in renal blood flow, which may precipitate overt renal decompensation. Patients at greatest risk of this reaction are those with impaired renal function, dehydration, hypovolemia, heart failure, liver dysfunction, those taking diuretics and ACE-inhibitors or ARBs, and the elderly. Discontinuation of NSAID therapy is usually followed by recovery to the pretreatment state.

No information is available from controlled clinical studies regarding the use of diclofenac sodium topical solution in patients with advanced renal disease. The renal effects of diclofenac sodium topical solution may hasten the progression of renal dysfunction in patients with preexisting renal disease.

Correct volume status in dehydrated or hypovolemic patients prior to initiating diclofenac sodium topical solution. Monitor renal function in patients with renal or hepatic impairment, heart failure, dehydration, or hypovolemia during use of diclofenac sodium topical solution [see Drug Interactions (7)]. Avoid the use of diclofenac sodium topical solution in patients with advanced renal disease unless the benefits are expected to outweigh the risk of worsening renal function. If diclofenac sodium topical solution is used in patients with advanced renal disease, monitor patients for signs of worsening renal function.

Hyperkalemia

Increases in serum potassium concentration, including hyperkalemia, have been reported with use of NSAIDs, even in some patients without renal impairment. In patients with normal renal function, these effects have been attributed to a hyporeninemic-hypoaldosteronism state

5.7 Anaphylactic Reactions

Diclofenac has been associated with anaphylactic reactions in patients with and without known hypersensitivity to diclofenac and in patients with aspirin-sensitive asthma [see Contraindications (4) and Warnings and Precautions (5.8)].

Seek emergency help if an anaphylactic reaction occurs.

5.8 Exacerbation of Asthma Related to Aspirin Sensitivity

A subpopulation of patients with asthma may have aspirin-sensitive asthma which may include chronic rhinosinusitis complicated by nasal polyps; severe, potentially fatal bronchospasm; and/or intolerance to aspirin and other NSAIDs. Because cross-reactivity between aspirin and other NSAIDs has been reported in such aspirin-sensitive patients, diclofenac sodium topical solution is contraindicated in patients with this form of aspirin sensitivity [see Contraindications (4)]. When diclofenac sodium topical solution is used in patients with preexisting asthma (without known aspirin sensitivity), monitor patients for changes in the signs and symptoms of asthma.

5.9 Serious Skin Reactions

NSAIDs, including diclofenac, can cause serious skin adverse reactions such as exfoliative dermatitis, Stevens-Johnson Syndrome (SJS), and toxic epidermal necrolysis (TEN), which can be fatal. These serious events may occur without warning. Inform patients about the signs and symptoms of serious skin reactions, and to discontinue the use of diclofenac sodium topical solution at the first appearance of skin rash or any other sign of hypersensitivity. Diclofenac sodium topical solution is contraindicated in patients with previous serious skin reactions to NSAIDs [see Contraindications (4)].

Do not apply diclofenac sodium topical solution to open skin wounds, infections, inflammations, or exfoliative dermatitis, as it may affect absorption and tolerability of the drug.

5.10 Drug Reaction with Eosinophilia and Systemic Symptoms (DRESS)

Drug Reaction with Eosinophilia and Systemic Symptoms (DRESS) has been reported in patients taking NSAIDs such as diclofenac sodium topical solution. Some of these events have been fatal or life-threatening. DRESS typically, although not exclusively, presents with fever, rash, lymphadenopathy, and/or facial swelling. Other clinical manifestations may include hepatitis, nephritis, hematological abnormalities, myocarditis, or myositis. Sometimes symptoms of DRESS may resemble an acute viral infection. Eosinophilia is often present. Because this disorder is variable in its presentation, other organ systems not noted here may be involved. It is important to note that early manifestations of hypersensitivity, such as fever or lymphadenopathy, may be present even though rash is not evident. If such signs or symptoms are present, discontinue diclofenac sodium topical solution and evaluate the patient immediately.

5.11 Fetal Toxicity

Premature Closure of Fetal Ductus Arteriosus

Avoid use of NSAIDs, including diclofenac sodium topical solution, in pregnant women at about 30 weeks gestation and later. NSAIDs, including diclofenac sodium topical solution, increase the risk of premature closure of the fetal ductus arteriosus at approximately this gestational age.

Oligohydramnios/Neonatal Renal Impairment

Use of NSAIDs, including diclofenac sodium topical solution, at about 20 weeks gestation or later in pregnancy may cause fetal renal dysfunction leading to oligohydramnios and, in some cases, neonatal renal impairment. These adverse outcomes are seen, on average, after days to weeks of treatment, although oligohydramnios has been infrequently reported as soon as 48 hours after NSAID initiation. Oligohydramnios is often, but not always, reversible with treatment discontinuation. Complications of prolonged oligohydramnios may, for example, include limb contractures and delayed lung maturation. In some postmarketing cases of impaired neonatal renal function, invasive procedures such as exchange transfusion or dialysis were required.

If NSAID treatment is necessary between about 20 and 30 weeks gestation, limit diclofenac sodium topical solution use to the lowest effective dose and shortest duration possible. Consider ultrasound monitoring of amniotic fluid if diclofenac sodium topical solution treatment extends beyond 48 hours. Discontinue diclofenac sodium topical solution if oligohydramnios occurs and follow up according to clinical practice [see Use in Specific Populations (8.1)].

5.12 Hematologic Toxicity

Anemia has occurred in NSAID-treated patients. This may be due to occult or gross blood loss, fluid retention, or an incompletely described effect on erythropoiesis. If a patient treated with diclofenac sodium topical solution has any signs or symptoms of anemia, monitor hemoglobin or hematocrit.

NSAIDs, including diclofenac sodium topical solution, may increase the risk of bleeding events. Co-morbid conditions such as coagulation disorders or concomitant use of warfarin, other anticoagulants, antiplatelet agents (e.g., aspirin), serotonin reuptake inhibitors (SSRIs) and serotonin norepinephrine reuptake inhibitors (SNRIs) may increase this risk. Monitor these patients for signs of bleeding [see Drug Interactions (7)].

5.13 Masking of Inflammation and Fever

The pharmacological activity of diclofenac sodium topical solution in reducing inflammation, and possibly fever, may diminish the utility of diagnostic signs in detecting infections.

5.14 Laboratory Monitoring

Because serious GI bleeding, hepatotoxicity, and renal injury can occur without warning symptoms or signs, consider monitoring patients on long-term NSAID treatment with a CBC and a chemistry profile periodically [see Warnings and Precautions (5.2, 5.3, 5.6)]

5.15 Sun Exposure

Instruct patients to avoid exposure to natural or artificial sunlight on treated knee(s) because studies in animals indicated topical diclofenac treatment resulted in an earlier onset of ultraviolet light-induced skin tumors. The potential effects of diclofenac sodium topical solution on skin response to ultraviolet damage in humans are not known.

5.16 Eye Exposure

Avoid contact of diclofenac sodium topical solution with eyes and mucosa. Advise patients that if eye contact occurs, immediately wash out the eye with water or saline and consult a physician if irritation persists for more than an hour.

5.17 Oral Nonsteroidal Anti-Inflammatory Drugs

Concomitant use of oral NSAIDs with diclofenac sodium topical solution, 1.5% resulted in a higher rate of rectal hemorrhage, more frequent abnormal creatinine, urea and hemoglobin. Therefore, do not use combination therapy with diclofenac sodium topical solution and an oral NSAID unless the benefit outweighs the risk and conduct periodic laboratory evaluations.

ADVERSE REACTIONS

The following adverse reactions are discussed in greater detail in other sections of the labeling:

Cardiovascular Thrombotic Events [see Warnings and Precautions (5.1)]
GI Bleeding, Ulceration and Perforation [see Warnings and Precautions (5.2)]
Hepatotoxicity [see Warnings and Precautions (5.3)]
Hypertension [see Warnings and Precautions (5.4)]
Heart Failure and Edema [see Warnings and Precautions (5.5)]
Renal Toxicity and Hyperkalemia [see Warnings and Precautions (5.6)]
Anaphylactic Reactions [see Warnings and Precautions (5.7)]
Serious Skin Reactions [see Warnings and Precautions (5.9)]
Hematologic Toxicity [see Warnings and Precautions (5.12)]

6.1 Clinical Trials Experience

Because clinical trials are conducted under widely varying conditions, adverse reaction rates observed in the clinical trials of a drug cannot be directly compared to rates in the clinical trials of another drug and may not reflect the rates observed in practice.

diclofenac sodium topical solution

The data described below reflect exposure to diclofenac sodium topical solution of 130 patients treated for 4 weeks (mean duration of 28 days) in one Phase 2 controlled trial. This population's mean age was approximately 60 years, 85% of patients were Caucasian, 65% were females, and all patients had primary osteoarthritis. The most common adverse events with diclofenac sodium topical solution were application site skin reactions. These events were the most common reason for withdrawing from the study.

Application Site Reactions:

In this controlled trial, application site reactions were characterized by one or more of the following: dryness (22%), exfoliation (7%), erythema (4%), pruritus (2%), pain (2%), induration (2%), rash (2%), and scabbing (<1%).

Other Common Adverse Reactions:

Table 1 lists all adverse reactions occurring in >1% of patients receiving diclofenac sodium topical solution, where the rate in the diclofenac sodium topical solution group exceeded vehicle, from a controlled study conducted in patients with osteoarthritis.

Table 1: Incidence of Adverse Reactions Occurring in >1% of Subjects with Osteoarthritis Using Diclofenac Sodium Topical Solution and More Often than in Subjects with OA Using Vehicle Control (Pooled)
Adverse Reaction
Diclofenac Sodium Topical Solution
N=130
n (%)
Vehicle Control
N=129
n (%)
Urinary tract infection
4 (3%)
1 (<1%)
Application site induration
2 (2%)
1 (<1%)
Contusion
2 (2%)
1 (<1%)
Sinus congestion
2 (2%)
1 (<1%)
Nausea
2 (2%)
0

Diclofenac Sodium Topical Solution 1.5%

The safety of diclofenac sodium topical solution 2% is based in part, on prior experience with diclofenac sodium topical solution 1.5%. The data described below reflect exposure to diclofenac sodium topical solution 1.5% of 911 patients treated between 4 and 12 weeks (mean duration of 49 days) in seven Phase 3 controlled trials, as well as exposure of 793 patients treated in an open-label study, including 463 patients treated for at least 6 months, and 144 patients treated for at least 12 months. The population mean age was approximately 60 years, 89% of patients were Caucasian, 64% were females, and all patients had primary osteoarthritis. The most common adverse events with diclofenac sodium topical solution 1.5% were application site skin reactions. These events were the most common reason for withdrawing from the studies.

Application Site Reactions:

In controlled trials, application site reactions were characterized by one or more of the following: dryness, erythema, induration, vesicles, paresthesia, pruritus, vasodilation, acne, and urticaria. The most frequent of these reactions were dry skin (32%), contact dermatitis characterized by skin erythema and induration (9%), contact dermatitis with vesicles (2%) and pruritus (4%). In one controlled trial, a higher rate of contact dermatitis with vesicles (4%) was observed after treatment of 152 subjects with the combination of diclofenac sodium topical solution 1.5% and oral diclofenac. In the open-label uncontrolled long-term safety study, contact dermatitis occurred in 13% and contact dermatitis with vesicles in 10% of patients, generally within the first 6 months of exposure, leading to a withdrawal rate for an application site event of 14%.

Other Common Adverse Reactions:

In controlled trials, subjects treated with diclofenac sodium topical solution 1.5% experienced some adverse events associated with the NSAID class more frequently than subjects using placebo (constipation, diarrhea, dyspepsia, nausea, flatulence, abdominal pain, edema; see Table 2). The combination of diclofenac sodium topical solution 1.5% and oral diclofenac, compared to oral diclofenac alone, resulted in a higher rate of rectal hemorrhage (3% vs. less than 1%), and more frequent abnormal creatinine (12% vs. 7%), urea (20% vs. 12%), and hemoglobin (13% vs. 9%), but no difference in elevation of liver transaminases.

Table 2 lists all adverse reactions occurring in ≥1% of patients receiving diclofenac sodium topical solution 1.5%, where the rate in the diclofenac sodium topical solution 1.5% group exceeded placebo, from seven controlled studies conducted in patients with osteoarthritis. Since these trials were of different durations, these percentages do not capture cumulative rates of occurrence.

Table 2: Adverse Reactions Occurring in ≥1% of Patients Treated with Diclofenac Sodium Topical Solution, 1.5% Topical Solution in Placebo and Oral Diclofenac-Controlled Trials
Treatment Group:
Diclofenac Sodium Topical Solution, 1.5%
N=911
Topical Placebo
N=332
Adverse Reaction
N (%)
N (%)
Dry Skin (Application Site)
292 (32)
17 (5)
Contact Dermatitis (Application Site)
83 (9)
6 (2)
Dyspepsia
72 (8)
13 (4)
Abdominal Pain
54 (6)
10 (3)
Flatulence
35 (4)
1 (<1)
Pruritus (Application Site)
34 (4)
7 (2)
Diarrhea
33 (4)
7 (2)
Nausea
33 (4)
3 (1)
Pharyngitis
40 (4)
13 (4)
Constipation
29 (3)
1 (<1)
Edema
26 (3)
0
Rash (Non-Application Site)
25 (3)
5 (2)
Infection
25 (3)
8 (2)
Ecchymosis
19 (2)
1 (<1)
Dry Skin (Non-Application Site)
19 (2)
1 (<1)
Contact Dermatitis, vesicles (Application Site)
18 (2)
0
Paresthesia (Non-Application Site)
14 (2)
3 (<1)
Accidental Injury
22 (2)
7 (2)
Pruritus (Non-Application Site)
15 (2)
2 (<1)
Sinusitis
10 (1)
2 (<1)
Halitosis
11 (1)
1 (<1)
Application Site Reaction (not otherwise specified)
11 (1)
3 (<1)

6.2 Postmarketing Experience

In postmarketing surveillance, the following adverse reactions have been reported during post-approval use of diclofenac sodium topical solution 1.5%. Because these reactions are reported voluntarily from a population of uncertain size, it is not always possible to reliably estimate their frequency or establish a causal relationship to drug exposure.

Body as a Whole:

abdominal pain, accidental injury, allergic reactions, asthenia, back pain, body odor, chest pain, edema, face edema, halitosis, headache, neck rigidity, pain

Cardiovascular:

palpitation, cardiovascular disorder

Gastrointestinal:

diarrhea, dry mouth, dyspepsia, gastroenteritis, decreased appetite, lip swelling, mouth ulceration, nausea, rectal hemorrhage, ulcerative stomatitis, swollen tongue

Metabolic and Nutritional:

creatinine increased

Musculoskeletal:

leg cramps, myalgia

Nervous:

depression, dizziness, drowsiness, lethargy, paresthesia at application site

Respiratory:

asthma, dyspnea, laryngismus, laryngitis, pharyngitis, throat swelling

Skin and Appendages:

At the Application Site: rash, skin burning sensation;

Other Skin and Appendages Adverse Reactions:

eczema, skin discoloration, urticaria

Special Senses:

abnormal vision, blurred vision, cataract, ear pain, eye disorder, eye pain, taste perversion

Vascular:

blood pressure increased, hypertension

DRUG INTERACTIONS

See Table 3 for clinically significant drug interactions with diclofenac.

Table 3: Clinically Significant Drug Interactions with Diclofenac
Drugs That Interfere with Hemostasis
Clinical Impact:
● Diclofenac and anticoagulants such as warfarin have a synergistic effect on bleeding. The concomitant use of diclofenac and anticoagulants have increased the risk of serious bleeding compared to the use of either drug alone.
● Serotonin release by platelets plays an important role in hemostasis. Case-control and cohort epidemiological studies showed that concomitant use of drugs that interfere with serotonin reuptake and an NSAID may potentiate the risk of bleeding more than an NSAID alone.
Intervention:
Monitor patients with concomitant use of diclofenac sodium topical solution with anticoagulants (e.g., warfarin), antiplatelet agents (e.g., aspirin), selective serotonin reuptake inhibitors (SSRIs), and serotonin norepinephrine reuptake inhibitors (SNRIs) for signs of bleeding [see Warnings and Precautions (5.12)].
Aspirin
Clinical Impact:
Controlled clinical studies showed that the concomitant use of NSAIDs and analgesic doses of aspirin does not produce any greater therapeutic effect than the use of NSAIDs alone. In a clinical study, the concomitant use of an NSAID and aspirin was associated with a significantly increased incidence of GI adverse reactions as compared to use of the NSAID alone [see Warnings and Precautions (5.2)].
Intervention:
Concomitant use of diclofenac sodium topical solution and analgesic doses of aspirin is not generally recommended because of the increased risk of bleeding [see Warnings and Precautions (5.12)].
Diclofenac sodium topical solution is not a substitute for low dose aspirin for cardiovascular protection.
ACE Inhibitors, Angiotensin Receptor Blockers, and Beta-Blockers
Clinical Impact:
● NSAIDs may diminish the antihypertensive effect of angiotensin converting enzyme (ACE) inhibitors, angiotensin receptor blockers (ARBs), or beta-blockers (including propranolol).
● In patients who are elderly, volume-depleted (including those on diuretic therapy), or have renal impairment, co-administration of an NSAID with ACE inhibitors or ARBs may result in deterioration of renal function, including possible acute renal failure. These effects are usually reversible.
Intervention:
● During concomitant use of diclofenac sodium topical solution and ACE-inhibitors, ARBs, or beta-blockers, monitor blood pressure to ensure that the desired blood pressure is obtained.
● During concomitant use of diclofenac sodium topical solution and ACE-inhibitors or ARBs in patients who are elderly, volume-depleted, or have impaired renal function, monitor for signs of worsening renal function [see Warnings and Precautions (5.6)].
● When these drugs are administered concomitantly, patients should be adequately hydrated. Assess renal function at the beginning of the concomitant treatment and periodically thereafter.
Diuretics
Clinical Impact:
Clinical studies, as well as post-marketing observations, showed that NSAIDs reduced the natriuretic effect of loop diuretics (e.g., furosemide) and thiazide diuretics in some patients. This effect has been attributed to the NSAID inhibition of renal prostaglandin synthesis.
Intervention:
During concomitant use of diclofenac sodium topical solution with diuretics, observe patients for signs of worsening renal function, in addition to assuring diuretic efficacy including antihypertensive effects [see Warnings and Precautions (5.6)].
Digoxin
Clinical Impact:
The concomitant use of diclofenac with digoxin has been reported to increase the serum concentration and prolong the half-life of digoxin.
Intervention:
During concomitant use of diclofenac sodium topical solution and digoxin, monitor serum digoxin levels.
Lithium
Clinical Impact:
NSAIDs have produced elevations in plasma lithium levels and reductions in renal lithium clearance. The mean minimum lithium concentration increased 15%, and the renal clearance decreased by approximately 20%. This effect has been attributed to NSAID inhibition of renal prostaglandin synthesis.
Intervention:
During concomitant use of diclofenac sodium topical solution and lithium, monitor patients for signs of lithium toxicity.
Methotrexate
Clinical Impact:
Concomitant use of NSAIDs and methotrexate may increase the risk for methotrexate toxicity (e.g., neutropenia, thrombocytopenia, renal dysfunction)
Intervention:
During concomitant use of diclofenac sodium topical solution and methotrexate, monitor patients for methotrexate toxicity.
Cyclosporine
Clinical Impact:
Concomitant use of diclofenac sodium topical solution and cyclosporine may increase cyclosporine's nephrotoxicity.
Intervention:
During concomitant use of diclofenac sodium topical solution and cyclosporine, monitor patients for signs of worsening renal function.
NSAIDs and Salicylates
Clinical Impact:
Concomitant use of diclofenac with other NSAIDs or salicylates (e.g., diflunisal, salsalate) increases the risk of GI toxicity, with little or no increase in efficacy [see Warnings and Precautions (5.2)]
Concomitant use of oral NSAIDs with diclofenac sodium topical solution has been evaluated in one Phase 3 controlled trial and in combination with oral diclofenac, compared to oral diclofenac alone, resulted in a higher rate of rectal hemorrhage (3% vs. less than 1%), and more frequent abnormal creatinine (12% vs. 7%), urea (20% vs. 12%) and hemoglobin (13% vs. 9%).
Intervention:
The concomitant use of diclofenac with other NSAIDs or salicylates is not recommended.
Do not use combination therapy with diclofenac sodium topical solution and an oral NSAID unless the benefit outweighs the risk and conduct periodic laboratory evaluations.
Pemetrexed
Clinical Impact:
Concomitant use of diclofenac sodium topical solution and pemetrexed may increase the risk of pemetrexed-associated myelosuppression, renal, and GI toxicity (see the pemetrexed prescribing information).
Intervention:
During concomitant use of diclofenac sodium topical solution and pemetrexed, in patients with renal impairment whose creatinine clearance ranges from 45 to 79 mL/min, monitor for myelosuppression, renal and GI toxicity.
NSAIDs with short elimination half-lives (e.g., diclofenac, indomethacin) should be avoided for a period of two days before, the day of, and two days following administration of pemetrexed.
In the absence of data regarding potential interaction between pemetrexed and NSAIDs with longer half-lives (e.g., meloxicam, nabumetone), patients taking these NSAIDs should interrupt dosing for at least five days before, the day of, and two days following pemetrexed administration.

USE IN SPECIFIC POPULATIONS

8.1 Pregnancy

Risk Summary

Use of NSAIDs, including diclofenac sodium topical solution, can cause premature closure of the fetal ductus arteriosus and fetal renal dysfunction leading to oligohydramnios and, in some cases, neonatal renal impairment. Because of these risks, limit dose and duration of diclofenac sodium topical solution use between about 20 and 30 weeks of gestation, and avoid diclofenac sodium topical solution use at about 30 weeks of gestation and later in pregnancy (see Clinical Considerations, Data).

Premature Closure of Fetal Ductus Arteriosus

Use of NSAIDs, including diclofenac sodium topical solution, at about 30 weeks gestation or later in pregnancy increases the risk of premature closure of the fetal ductus arteriosus.

Oligohydramnios/Neonatal Renal Impairment

Use of NSAIDs at about 20 weeks gestation or later in pregnancy has been associated with cases of fetal renal dysfunction leading to oligohydramnios, and in some cases, neonatal renal impairment.

Data from observational studies regarding other potential embryofetal risks of NSAID use in women in the first or second trimesters of pregnancy are inconclusive. In animal reproduction studies, no evidence of malformations were observed in mice, rats, or rabbits given diclofenac during the period of organogenesis at doses up to approximately 0.6, 0.6, and 1.3 times, respectively, the maximum recommended human dose (MRHD) of 162 mg diclofenac sodium via diclofenac sodium topical solution, despite the presence of maternal and fetal toxicity at these doses [see Data]. Based on animal data, prostaglandins have been shown to have an important role in endometrial vascular permeability, blastocyst implantation, and decidualization. In animal studies, administration of prostaglandin synthesis inhibitors such as diclofenac, resulted in increased pre- and post-implantation loss. Prostaglandins also have been shown to have an important role in fetal kidney development. In published animal studies, prostaglandin synthesis inhibitors have been reported to impair kidney development when administered at clinically relevant doses.

The estimated background risk of major birth defects and miscarriage for the indicated population(s) is unknown. All pregnancies have a background risk of birth defect, loss, or other adverse outcomes. In the U.S. general population, the estimated background risk of major birth defects and miscarriage in clinically recognized pregnancies is 2% to 4% and 15% to 20%, respectively.

Clinical Considerations

Fetal/Neonatal Adverse Reactions

Premature Closure of the Fetal Ductus Arteriosus:

Avoid use of NSAIDs in women at about 30 weeks gestation and later in pregnancy, because NSAIDs, including diclofenac sodium topical solution, can cause premature closure of the fetal ductus arteriosus (see Data).

Oligohydramnios/Neonatal Renal Impairment:

If an NSAID is necessary at about 20 weeks gestation or later in pregnancy, limit the use to the lowest effective dose and shortest duration possible. If diclofenac sodium topical solution treatment extends beyond 48 hours, consider monitoring with ultrasound for oligohydramnios. If oligohydramnios occurs, discontinue diclofenac sodium topical solution and follow up according to clinical practice (see Data).

Labor or Delivery:

There are no studies on the effects of diclofenac sodium topical solution during labor or delivery. In animal studies, NSAIDs, including diclofenac inhibit prostaglandin synthesis, cause delayed parturition, and increase the incidence of stillbirth.

Data

Human Data

Premature Closure of Fetal Ductus Arteriosus:

Published literature reports that the use of NSAIDs at about 30 weeks of gestation and later in pregnancy may cause premature closure of the fetal ductus arteriosus.

Oligohydramnios/Neonatal Renal Impairment:

Published studies and postmarketing reports describe maternal NSAID use at about 20 weeks gestation or later in pregnancy associated with fetal renal dysfunction leading to oligohydramnios, and in some cases, neonatal renal impairment. These adverse outcomes are seen, on average, after days to weeks of treatment, although oligohydramnios has been infrequently reported as soon as 48 hours after NSAID initiation. In many cases, but not all, the decrease in amniotic fluid was transient and reversible with cessation of the drug. There have been a limited number of case reports of maternal NSAID use and neonatal renal dysfunction without oligohydramnios, some of which were irreversible. Some cases of neonatal renal dysfunction required treatment with invasive procedures, such as exchange transfusion or dialysis.

Methodological limitations of these postmarketing studies and reports include lack of a control group; limited information regarding dose, duration, and timing of drug exposure; and concomitant use of other medications. These limitations preclude establishing a reliable estimate of the risk of adverse fetal and neonatal outcomes with maternal NSAID use. Because the published safety data on neonatal outcomes involved mostly preterm infants, the generalizability of certain reported risks to the full-term infant exposed to NSAIDs through maternal use is uncertain.

Animal data:

Reproductive and developmental studies in animals demonstrated that diclofenac sodium administration during organogenesis did not produce malformations despite the induction of maternal toxicity and fetal toxicity in mice at oral doses up to 20 mg/kg/day (approximately 0.6 times the maximum recommended human dose [MRHD] of diclofenac sodium topical solution, 162 mg diclofenac sodium/day, based on body surface area (BSA) comparison), and in rats and rabbits at oral doses up to 10 mg/kg/day (approximately 0.6 and 1.3-times, respectively, the MRHD based on BSA comparison). Published reproductive and developmental studies of dimethyl sulfoxide (DMSO, the solvent used in diclofenac sodium topical solution) are equivocal as to potential teratogenicity.

In a study in which pregnant rats were orally administered 2 or 4 mg/kg diclofenac (0.12 and 0.24 times the MRHD, respectively, based on BSA comparison) from Gestation Day 15 through Lactation Day 21, significant maternal toxicity (peritonitis, mortality) was noted. These maternally toxic doses were associated with dystocia, prolonged gestation, reduced fetal weights and growth, and reduced fetal survival. Diclofenac has been shown to cross the placental barrier in mice and rats.

In published studies, diclofenac administration to pregnant rats prolonged gestation and produced liver toxicity and neuronal loss in offspring (1 mg/kg, IP; 0.06 times the MRHD based on BSA comparison), impaired nephrogenesis in the kidney (3.6 mg/kg, IP; 0.2 times the MRHD based on BSA comparison), and caused adverse effects on the developing testes (6.1 mg/kg, oral; 0.4 times the MRHD based on BSA comparison).

8.2 Lactation

Risk Summary

Based on available data, diclofenac may be present in human milk. The developmental and health benefits of breastfeeding should be considered along with the mother's clinical need for diclofenac sodium topical solution and any potential adverse effects on the breastfed infant from the diclofenac sodium topical solution or from the underlying maternal condition.

Data

One woman treated orally with a diclofenac salt, 150 mg/day, had a milk diclofenac level of 100 mcg/L, equivalent to an infant dose of about 0.03 mg/kg/day. Diclofenac was not detectable in breast milk in 12 women using diclofenac (after either 100 mg/day orally for 7 days or a single 50 mg intramuscular dose administered in the immediate postpartum period).

8.3 Females and Males of Reproductive Potential

Infertility

Females:

Based on the mechanism of action, the use of prostaglandin-mediated NSAIDs, including diclofenac sodium topical solution, may delay or prevent rupture of ovarian follicles, which has been associated with reversible infertility in some women. Published animal studies have shown that administration of prostaglandin synthesis inhibitors has the potential to disrupt prostaglandin-mediated follicular rupture required for ovulation. Small studies in women treated with NSAIDs have also shown a reversible delay in ovulation. Consider withdrawal of NSAIDs, including diclofenac sodium topical solution, in women who have difficulties conceiving or who are undergoing investigation of infertility.

Males:

Published studies in adult male rodents report that diclofenac, at clinically relevant doses, can produce adverse effects on male reproductive tissues. The impact of these findings on male fertility is not clear [See Nonclinical Toxicology (13.1)].

8.4 Pediatric Use

Safety and effectiveness in pediatric patients have not been established.

8.5 Geriatric Use

Elderly patients, compared to younger patients, are at greater risk for NSAID-associated serious cardiovascular, gastrointestinal, and/or renal adverse reactions. If the anticipated benefit for the elderly patient outweighs these potential risks, start dosing at the low end of the dosing range, and monitor patients for adverse effects [see Warnings and Precautions (5.1, 5.2, 5.3, 5.6, 5.14)].

Of the 911 patients treated with diclofenac sodium topical solution 1.5% in seven controlled, Phase 3 clinical trials, 444 subjects were 65 years of age and over. There was no age-related difference in the incidence of adverse events. Of the 793 patients treated with diclofenac sodium topical solution 1.5% in one open-labeled safety trial, 334 subjects were 65 years of age and over including 107 subjects 75 and over. There was no difference in the incidence of adverse events with long-term exposure to diclofenac sodium topical solution 1.5% for this elderly population.

OVERDOSAGE

Symptoms following acute NSAID overdosages have been typically limited to lethargy, drowsiness, nausea, vomiting, and epigastric pain, which have been generally reversible with supportive care. Gastrointestinal bleeding has occurred. Hypertension, acute renal failure, respiratory depression, and coma have occurred but were rare [see Warnings and Precautions (5.1, 5.2, 5.4, 5.6)].

Manage patients with symptomatic and supportive care following an NSAID overdosage. There are no specific antidotes. Emesis is not recommended due to a possibility of aspiration and subsequent respiratory irritation by DMSO contained in diclofenac sodium topical solution. Consider activated charcoal (60 to 100 grams in adults, 1 to 2 grams per kg of body weight in pediatric patients) and/or osmotic cathartic in symptomatic patients seen within four hours of ingestion or in patients with a large overdosage (5 to 10 times the recommended dosage). Forced diuresis, alkalinization of urine, hemodialysis, or hemoperfusion may not be useful due to high protein binding.

For additional information about overdosage treatment, contact a poison control center (1-800-222-1222).

DESCRIPTION

Diclofenac sodium topical solution 2%, contains diclofenac sodium, a benzeneacetic acid derivative that is a nonsteroidal anti-inflammatory drug, and is available as a clear, colorless to faintly pink or orange solution for topical application. The chemical name is 2-[(2,6-dichlorophenyl)amino]-benzeneacetic acid, monosodium salt. The molecular weight is 318.14. Its molecular formula is C14H10Cl2NNaO2 and it has the following chemical structure.

[Figure 1]

Each 1 gram of solution contains 20 mg of diclofenac sodium. The inactive ingredients: dimethyl sulfoxide USP (DMSO, 45.5% w/w), ethanol, purified water, propylene glycol, and hydroxypropyl cellulose.

CLINICAL PHARMACOLOGY

12.1 Mechanism of Action

Diclofenac has analgesic, anti-inflammatory, and antipyretic properties.

The mechanism of action of diclofenac sodium topical solution, like that of other NSAIDs, is not completely understood but involves inhibition of cyclooxygenase (COX-1 and COX-2).

Diclofenac is a potent inhibitor of prostaglandin synthesis in vitro. Diclofenac concentrations reached during therapy have produced in vivo effects. Prostaglandins sensitize afferent nerves and potentiate the action of bradykinin in inducing pain in animal models. Prostaglandins are mediators of inflammation. Because diclofenac is an inhibitor of prostaglandin synthesis, its mode of action may be due to a decrease of prostaglandins in peripheral tissues.

12.3 Pharmacokinetics

Absorption

After administration of diclofenac sodium topical solution (40 mg/knee every 12 h; total daily diclofenac exposure: 80 mg/knee) for 7.5 days, the mean (SD) AUC0-12 and mean (SD) Cmax were 77.27 (49.89) ng•h/mL and 12.16 (7.66) ng/mL, respectively, on Day 1; and 204.58 (111.02) ng•h/mL and 25.24 (12.95) ng/mL, respectively, at steady state on Day 8. After administration of diclofenac sodium topical solution, 1.5% topical solution (19.3 mg/knee every 6 h; total daily diclofenac exposure 77.2 mg/knee), the mean (SD) AUC0-12 and mean (SD) Cmax were 27.46 (23.97) ng•h/mL and 2.30 (2.02) ng/mL, respectively, on Day 1; and 141.49 (92.47) ng•h/mL and 17.04 (11.28) ng/mL, respectively, at steady state on Day 8.

The pharmacokinetics and effect of diclofenac sodium topical solution were not evaluated under the conditions of heat application, occlusive dressings overlay, or exercise following product application. Therefore, concurrent use of diclofenac sodium topical solution under these conditions is not recommended.

Distribution

Diclofenac is more than 99% bound to human serum proteins, primarily to albumin.

Diclofenac diffuses into and out of the synovial fluid. Diffusion into the joint occurs when plasma levels are higher than those in the synovial fluid, after which the process reverses and synovial fluid levels are higher than plasma levels. It is not known whether diffusion into the joint plays a role in the effectiveness of diclofenac.

Elimination

Metabolism:

Five diclofenac metabolites have been identified in human plasma and urine. The metabolites include 4'-hydroxy-, 5-hydroxy-, 3'-hydroxy-, 4',5-dihydroxy- and 3'-hydroxy-4'-methoxy diclofenac. The major diclofenac metabolite, 4'-hydroxy-diclofenac, has very weak pharmacologic activity. The formation of 4'-hydroxy diclofenac is primarily mediated by CYP2C9. Both diclofenac and its oxidative metabolites undergo glucuronidation or sulfation followed by biliary excretion. Acylglucuronidation mediated by UGT2B7 and oxidation mediated by CYP2C8 may also play a role in diclofenac metabolism. CYP3A4 is responsible for the formation of minor metabolites, 5-hydroxy and 3'-hydroxy-diclofenac.

Excretion:

Diclofenac is eliminated through metabolism and subsequent urinary and biliary excretion of the glucuronide and the sulfate conjugates of the metabolites.

Little or no free unchanged diclofenac is excreted in the urine.

Specific Populations

Pediatric:

The pharmacokinetics of diclofenac sodium topical solution has not been investigated in pediatric patients.

Race:

Pharmacokinetic differences due to race have not been studied.

Drug Interaction Studies

Aspirin:

When NSAIDs were administered with aspirin, the protein binding of NSAIDs were reduced, although the clearance of free NSAID was not altered. The clinical significance of this interaction is not known. See Table 3 for clinically significant drug interactions of NSAIDs with aspirin [see Drug Interactions (7)].

NONCLINICAL TOXICOLOGY

13.1 Carcinogenesis, Mutagenesis, Impairment of Fertility

Carcinogenesis

Carcinogenicity studies in mice and rats administered diclofenac sodium as a dietary constituent for 2 years resulted in no significant increases in tumor incidence at doses up to 2 mg/kg/day approximately 0.85 and 1.7 times, respectively, the maximum recommended human topical dose of diclofenac sodium topical solution (based on apparent bioavailability and body surface area comparison).

In a dermal carcinogenicity study conducted in albino mice, daily topical applications of diclofenac sodium for two years at concentrations up to 0.035% diclofenac sodium (a 57-fold lower diclofenac sodium concentration than present in diclofenac sodium topical solution) did not increase neoplasm incidence.

In a photococarcinogenicity study conducted in hairless mice, topical application of diclofenac sodium at doses up to 0.035% diclofenac sodium (a 57-fold lower diclofenac sodium concentration than present in diclofenac sodium topical solution) resulted in an earlier median time of onset of tumors.

Mutagenesis

Diclofenac was not mutagenic or clastogenic in a battery of genotoxicity tests that included the bacterial reverse mutation assay, in vitro mouse lymphoma point mutation assay, chromosomal aberration studies in Chinese hamster ovarian cells in vitro, and in vivo rat chromosomal aberration assay of bone marrow cells.

Impairment of Fertility

Fertility studies have not been conducted with diclofenac sodium topical solution. Diclofenac sodium administered to male and female rats at doses up to 4 mg/kg/day (approximately 3.4 times the MRHD of diclofenac sodium topical solution based on apparent bioavailability and body surface area comparison) did not affect fertility. Studies conducted in rats found no effect of dermally applied DMSO on fertility, reproductive performance, or offspring performance.

However, published studies report that treatment of adult male rats with diclofenac by the oral route at 10 mg/kg (0.6 times the MRHD) for 14 days and at 0.25 mg/kg (0.01 times the MRHD) for 30 days produced adverse effects on male reproductive hormones and testes.

13.2 Animal Toxicology and/or Pharmacology

Ocular Effects

No adverse effects were observed using indirect ophthalmoscopy after multiple-daily dermal application to rats for 26 weeks and minipigs for 52 weeks of DMSO at twice the concentration found in diclofenac sodium topical solution. Published studies of dermal or oral administration of DMSO to rabbits, dogs and pigs described refractive changes of lens curvature and cortical fibers indicative of myopic changes and/or incidences of lens opacity or discoloration when evaluated using slit-lamp biomicroscopy examination, although no ocular abnormalities were observed in rhesus monkeys during daily oral or dermal treatment with DMSO for 9 to 18 months.

CLINICAL STUDIES

14.1 Study in Osteoarthritis of the Knee

Diclofenac Sodium Topical Solution

The use of diclofenac sodium topical solution for the treatment of pain of osteoarthritis of the knee was evaluated in a single double-blind controlled trial conducted in the US, involving patients treated with diclofenac sodium topical solution at a dose of 2 pumps twice a day for 4 weeks. Diclofenac sodium topical solution was compared to topical vehicle, applied directly to the study knee. In this trial, patients treated with diclofenac sodium topical solution experienced a greater reduction in the Western Ontario and McMaster Universities Osteoarthritis Index (WOMAC) pain subscale compared to patients treated with vehicle. Numerical results of the WOMAC pain subscale are summarized in Table 4.

Table 4: Change in Treatment Outcomes after 4 Weeks of Treatment with Diclofenac Sodium Topical Solution

*
WOMAC pain subscale is based on the sum of pain scores for five items using a 5-point Likert scale.

HOW SUPPLIED

Diclofenac sodium topical solution 2% w/w, is supplied as a clear, colorless to faintly pink or orange solution containing 20 mg of diclofenac sodium per gram of solution, in a white polypropylene-dose pump bottle with a clear cap. Each pump actuation delivers 20 mg of diclofenac sodium in 1 gram of solution.

NDC Number & Size

112 g bottle……………………………………….NDC # 72189-509-04

Storage

Store at 25°C (77°F); excursions permitted to 15° to 30°C (59° to 86°F) [see USP Controlled Room Temperature].

PATIENT COUNSELING INFORMATION

Advise the patient to read the FDA-approved patient labeling (Medication Guide) that accompanies each prescription dispensed. Inform patients, families, or their caregivers of the following information before initiating therapy with diclofenac sodium topical solution and periodically during the course of ongoing therapy.

Cardiovascular Thrombotic Events

Advise patients to be alert for the symptoms of cardiovascular thrombotic events, including chest pain, shortness of breath, weakness, or slurring of speech, and to report any of these symptoms to their health care provider immediately [see Warnings and Precautions (5.1)].

Gastrointestinal Bleeding, Ulceration, and Perforation

Advise patients to report symptoms of ulceration and bleeding, including epigastric pain, dyspepsia, melena, and hematemesis to their health care provider. In the setting of concomitant use of low-dose aspirin for cardiac prophylaxis, inform patients of the increased risk for and the signs and symptoms of GI bleeding [see Warnings and Precautions (5.2)].

Hepatotoxicity

Inform patients of the warning signs and symptoms of hepatotoxicity (e.g., nausea, fatigue, lethargy, pruritus, jaundice, right upper quadrant tenderness, and "flu-like" symptoms). If these occur, instruct patients to stop diclofenac sodium topical solution and seek immediate medical therapy [see Warnings and Precautions (5.3)].

Heart Failure and Edema

Advise patients to be alert for the symptoms of congestive heart failure including shortness of breath, unexplained weight gain, or edema and to contact their healthcare provider if such symptoms occur [see Warnings and Precautions (5.5)].

Anaphylactic Reactions

Inform patients of the signs of an anaphylactic reaction (e.g., difficulty breathing, swelling of the face or throat). Instruct patients to seek immediate emergency help if these occur [see Contraindications (4) and Warnings and Precautions (5.7)].

Serious Skin Reactions, including DRESS

Advise patients to stop using diclofenac sodium topical solution immediately if they develop any type of rash or fever and contact their health care provider as soon as possible [see Warnings and Precautions (5.9, 5.10)].

Female Fertility

Advise females of reproductive potential who desire pregnancy that NSAIDs, including diclofenac sodium topical solution, may be associated with a reversible delay in ovulation [see Use in Specific Populations (8.3)]

Fetal Toxicity

Inform pregnant women to avoid use of diclofenac sodium topical solution and other NSAIDs starting at 30 weeks gestation because of the risk of the premature closing of the fetal ductus arteriosus [see Warnings and Precautions (5.11)]. If treatment with diclofenac sodium topical solution is needed for a pregnant woman between about 20 to 30 weeks gestation, advise her that she may need to be monitored for oligohydramnios, if treatment continues for longer than 48 hours [see Warnings and Precautions (5.11) and Use in Specific Populations (8.1)].

Avoid Concomitant Use of NSAIDs

Inform patients that the concomitant use of diclofenac sodium topical solution with other NSAIDs or salicylates (e.g., diflunisal, salsalate) is not recommended due to the increased risk of gastrointestinal toxicity, and little or no increase in efficacy [see Warnings and Precautions (5.2) and Drug Interactions (7)]. Alert patients that NSAIDs may be present in "over the counter" medications for treatment of colds, fever, or insomnia.

Use of NSAIDs and Low-Dose Aspirin

Inform patients not to use low-dose aspirin concomitantly with diclofenac sodium topical solution until they talk to their healthcare provider [see Drug Interactions (7)].

Eye Exposure

Instruct patients to avoid contact of diclofenac sodium topical solution with the eyes and mucosa. Advise patients that if eye contact occurs, immediately wash out the eye with water or saline and consult a physician if irritation persists for more than an hour.

Prevention of Secondary Exposure

Instruct patients to avoid skin-to-skin contact between other people and the knee(s) to which diclofenac sodium topical solution was applied until the knee(s) is completely dry.

Special Application Instructions

Instruct patients not to apply diclofenac sodium topical solution to open skin wounds, infections, inflammations, or exfoliative dermatitis, as it may affect absorption and reduce tolerability of the drug.

Instruct patients to wait until the area treated with diclofenac sodium topical solution is completely dry before applying sunscreen, insect repellant, lotion, moisturizer, cosmetics, or other topical medication.

Instruct patients to minimize or avoid exposure of treated knee(s) to natural or artificial sunlight.

Distributed by:

Lupin Pharmaceuticals, Inc.

Baltimore, Maryland 21202

United States

ID# : 271266

Medication Guide for Nonsteroidal Anti-inflammatory Drugs (NSAIDs)

What is the most important information I should know about medicines called Nonsteroidal Anti-inflammatory Drugs (NSAIDs)?

NSAIDs can cause serious side effects, including:

Increased risk of a heart attack or stroke that can lead to death. This risk may happen early in treatment and may increase:

with increasing doses of NSAIDs
with longer use of NSAIDs

Do not take NSAIDs right before or after a heart surgery called a "coronary artery bypass graft (CABG)."

Avoid taking NSAIDs after a recent heart attack, unless your healthcare provider tells you to. You may have an increased risk of another heart attack if you take NSAIDs after a recent heart attack.

Increased risk of bleeding, ulcers, and tears (perforation) of the esophagus (tube leading from the mouth to the stomach), stomach and intestines:

anytime during use
without warning symptoms
that may cause death

The risk of getting an ulcer or bleeding increases with:

past history of stomach ulcers, or stomach or intestinal bleeding with use of NSAIDs
taking medicines called "corticosteroids", "anticoagulants", "SSRIs", or "SNRIs"
increasing doses of NSAIDs
longer use of NSAIDs
smoking
drinking alcohol
older age
poor health
advanced liver disease
bleeding problems

NSAIDs should only be used:

exactly as prescribed
at the lowest dose possible for your treatment
for the shortest time needed

What are NSAIDs?

NSAIDs are used to treat pain and redness, swelling, and heat (inflammation) from medical conditions such as different types of arthritis, menstrual cramps, and other types of short-term pain.

Who should not take NSAIDs?

Do not take NSAIDs:

if you have had an asthma attack, hives, or other allergic reaction with aspirin or any other NSAIDs
right before or after heart bypass surgery.

Before taking NSAIDs, tell your health care provider about all of your medical conditions, including if you:

have liver or kidney problems
have high blood pressure
have asthma
are pregnant or plan to become pregnant. Taking NSAIDs at about 20 weeks of pregnancy or later may harm your unborn baby. If you need to take NSAIDs for more than 2 days when you are between 20 and 30 weeks of pregnancy, your healthcare provider may need to monitor the amount of fluid in your womb around your baby. You should not take NSAIDs after about 30 weeks of pregnancy.
are breastfeeding or plan to breast feed.

Tell your health care provider about all of the medicines you take, including prescription or over-the-counter medicines, vitamins or herbal supplements. NSAIDs and some other medicines can interact with each other and cause serious side effects. Do not start taking new medicine without talking to your health care provider first.

What are the possible side effects of NSAIDs?

NSAIDs can cause serious side effects, including:

See "What is the most important information I should know about medicines called Nonsteroidal Anti-inflammatory Drugs (NSAIDs)?"

new or worse high blood pressure
heart failure
liver problems including liver failure
kidney problems including kidney failure
low red blood cells (anemia)
life-threatening skin reactions
life-threatening allergic reactions
Other side effects of NSAIDs include: stomach pain, constipation, diarrhea, gas, heartburn, nausea, vomiting and dizziness.

Get emergency help right away if you get any of the following symptoms:

shortness of breath or trouble breathing
chest pain
weakness in one part or side of your body
slurred speech
swelling of the face or throat

Stop taking your NSAID and call your health care provider right away if you get any of the following symptoms:

nausea
more tired or weaker than usual
diarrhea
itching
your skin or eyes look yellow
indigestion or stomach pain
flu-like symptoms
vomit blood
there is blood in your bowel movement or it is black and sticky like tar
unusual weight gain
skin rash or blisters with fever
swelling of the arms, legs, hands, and feet

If you take too much of your NSAID, call your health care provider or get medical help right away. These are not all the possible side effects of NSAIDs. For more information, ask your health care provider or pharmacist about NSAIDs.

Call your doctor for medical advice about side effects. You may report side effects to FDA at 1-800-FDA-1088.

Other information about NSAIDs

Aspirin is an NSAID but it does not increase the chance of a heart attack. Aspirin can cause bleeding in the brain, stomach, and intestines. Aspirin can also cause ulcers in the stomach and intestines.
Some NSAIDs are sold in lower doses without a prescription (over-the-counter). Talk to your health care provider before using over-the-counter NSAIDs for more than 10 days.

General information about the safe and effective use of NSAIDs

Medicines are sometimes prescribed for purposes other than those listed in a Medication Guide. Do not use NSAIDs for a condition for which it was not prescribed. Do not give NSAIDs to other people, even if they have the same symptoms that you have. It may harm them.

If you would like more information about NSAIDs, talk with your health care provider. You can ask your pharmacist or health care provider for information about NSAIDs that is written for health professionals.

Distributed by: Lupin Pharmaceuticals, Inc, Baltimore, Maryland 21202, United States

For more information, call 1-800-399-2561.

This Medication Guide has been approved by the U.S. Food and Drug Administration. Revised 01/2022

Instructions for Use

DICLOFENAC (dye-KLOE-fen-ak)

SODIUM TOPICAL SOLUTION, 2 % w/w

Read the Medication Guide that comes with diclofenac sodium topical solution first. Be sure that you read, understand and follow these Instructions for Use before you use diclofenac sodium topical solution for the first time.

Important: For use on the skin only (topical). Do not get diclofenac sodium topical solution in your eyes, nose or mouth.

Before you use diclofenac sodium topical solution:

Apply diclofenac sodium topical solution exactly as your healthcare provider tells you. Talk with your healthcare provider or pharmacist if you are not sure.
Only use diclofenac sodium topical solution to treat pain from osteoarthritis in your knee or knees.
Apply diclofenac sodium topical solution on clean, dry skin that does not have any cuts, infections or rashes.
Use diclofenac sodium topical solution two times a day on your knee or knees as prescribed.
If you get diclofenac sodium topical solution in your eyes, rinse your eyes right away with water or saline. Call your healthcare provider if your eyes are irritated for more than one hour.

Diclofenac sodium topical solution comes in a pump bottle or in a sample packet from your healthcare provider

If you are using a diclofenac sodium topical solution pump bottle follow the steps below:

Before you use diclofenac sodium topical solution pump bottle for the first time, you will need to prime the pump. To prime the pump, remove the cap (See Figure A) and fully press the top of the pump all the way down 4 times while holding the bottle in an upright position (See Figure B). Dispense this portion of the medicine into a tissue or paper towel and throw it away in a trash can. The pump is now ready to use. You should not need to prime the pump again.

[image 1]

Figure A.

[image 2]

Figure B.

Steps for using diclofenac sodium topical solution pump bottle:

Step 1: Wash your hands with soap and water before applying diclofenac sodium topical solution.

Step 2: Remove the bottle cap and press the pump head down firmly and fully to dispense diclofenac sodium topical solution into the palm of your hand. Release the pump head and then press the pump head down firmly and fully a second time. When you use your diclofenac sodium topical solution pump bottle, you can hold the bottle at an angle. Put 2 pumps of diclofenac sodium topical solution on your hand (See Figure C).

[image 3]

Figure C.

Step 3: Apply diclofenac sodium topical solution evenly around the front, back, and sides of your knee. Diclofenac sodium topical solution should be applied without massaging the knee (See Figures D and E).

[image 4]

Figure D.

[image 5]

Figure E.

Step 4: Repeat Steps 2 and 3 for your other knee if your healthcare provider has prescribed diclofenac sodium topical solution for both knees.

Step 5: Wash your hands with soap and water right away after applying diclofenac sodium topical solution.

Step 6: Replace the cap on the bottle and store in an upright position.

If you are using a diclofenac sodium topical solution sample packet follow the steps below:

Steps for using a diclofenac sodium topical solution sample packet:

Step 1: Wash your hands with soap and water before applying diclofenac sodium topical solution.

Step 2: Cut open the sample packet using scissors or completely tear the packet at the notch on the dotted line (See Figure A). Do not use your teeth to open the sample packet (See Figure A).

[Figure A]

Figure A.

Step 3: Squeeze from the bottom of the sample packet to the top to remove contents. Squeeze all of the diclofenac sodium

topical solution out of the sample packet into the palm of your hand (See Figure B).

[Figure B]

Figure B.

Step 4: Apply diclofenac sodium topical solution evenly around the front, back, and sides of your knee. Diclofenac sodium topical solution should be applied without massaging the knee (See Figures C and D).

[Figure C and D]

Step 5: Repeat steps 2 through 4 for your other knee if your healthcare provider has prescribed diclofenac sodium topical solution for both knees.

Step 6: Wash your hands with soap and water right away after applying diclofenac sodium topical solution.

Step 7: Throw away the empty sample packet into a trash can.

After you use diclofenac sodium topical solution:

Do not:

cover your knee with clothing until your knee is completely dry.
put sunscreen, insect repellant, lotion, moisturizer, cosmetics, or other topical medicines on your knee until it is completely dry.
take a shower or a bath for at least 30 minutes after you put diclofenac sodium topical solution on your knee(s).
use heating pads or cover the treated area with bandages where you have applied diclofenac sodium topical solution.
exercise following application of diclofenac sodium topical solution.
use sunlamp and tanning beds. Protect your treated knee from sunlight. Wear clothes that cover your skin if you have to be in the sunlight.

How should I store diclofenac sodium topical solution?

Store diclofenac sodium topical solution at room temperature between 68°F to 77°F (20°C to 25°C).

Keep diclofenac sodium topical solution and all medicines out of the reach of children.

This Instructions for Use has been approved by the U.S. Food and Drug Administration.

Distributed by:

Lupin Pharmaceuticals, Inc.

Baltimore, Maryland 21202

United States

Revised: 01/2022